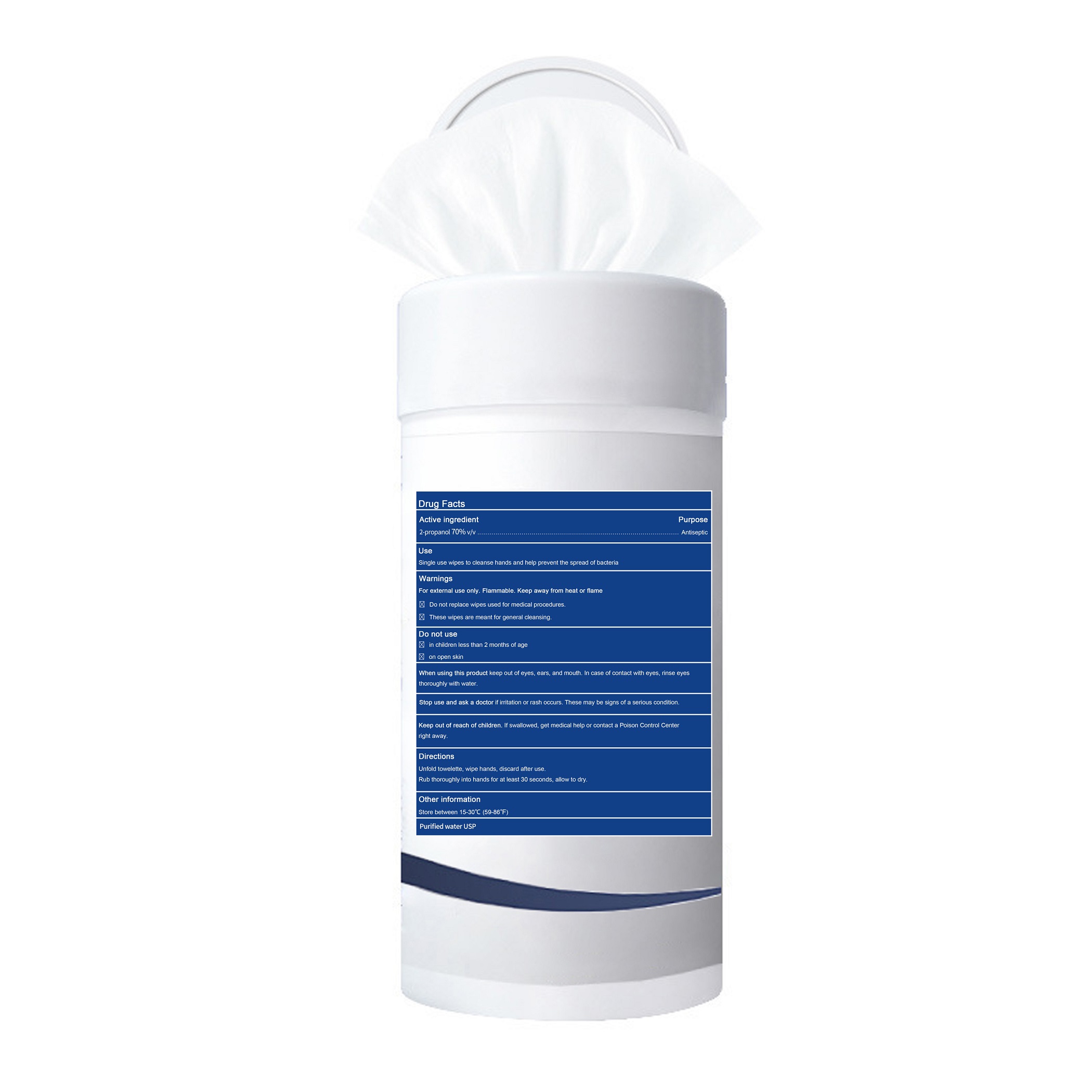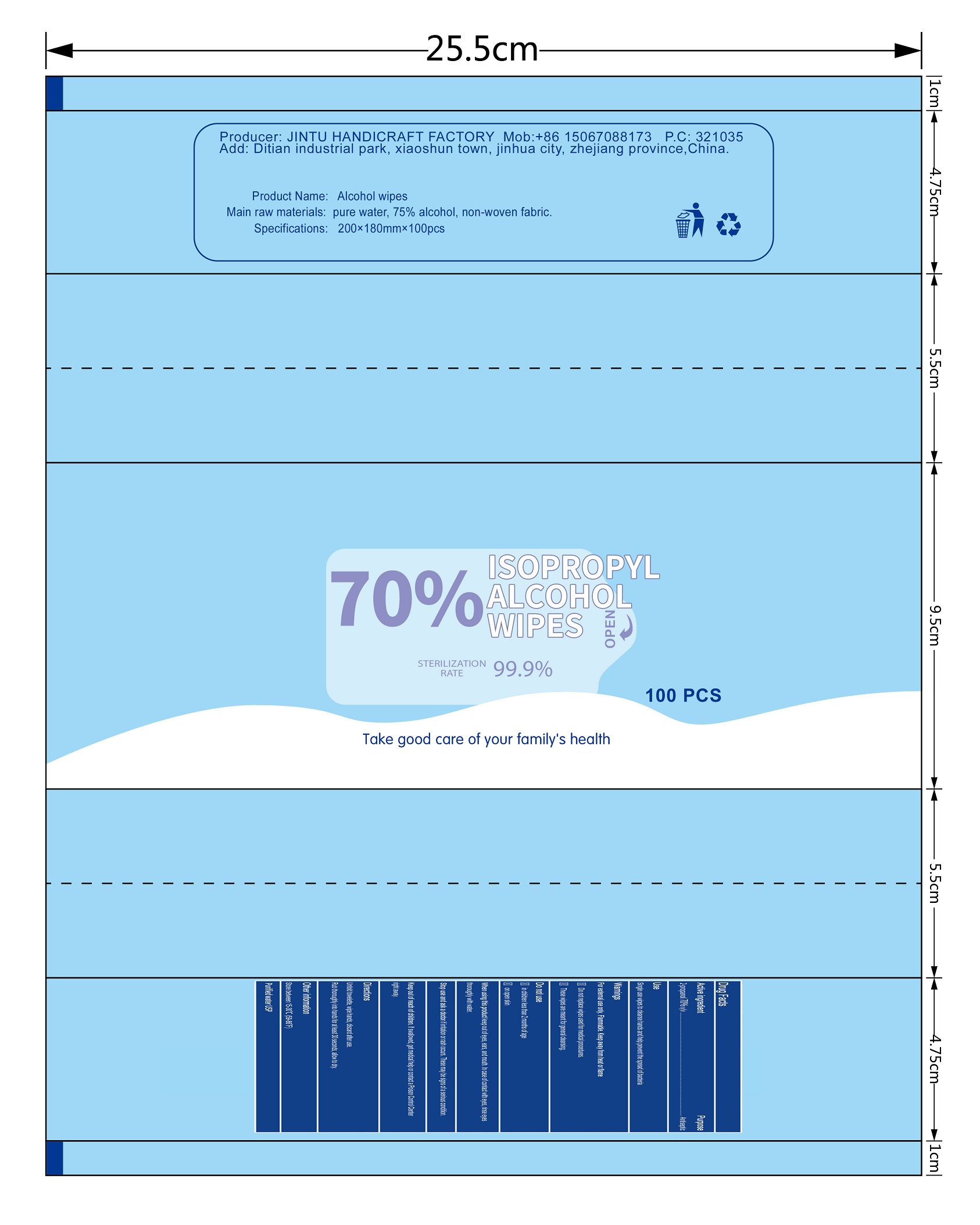 DRUG LABEL: Isopropyl alcohol wipes
NDC: 79846-121 | Form: CLOTH
Manufacturer: Jintu Handicraft Factory
Category: otc | Type: HUMAN OTC DRUG LABEL
Date: 20200906

ACTIVE INGREDIENTS: ISOPROPYL ALCOHOL 2.8 mL/1 1
INACTIVE INGREDIENTS: WATER

JinTu, Wipes, 70% Isopropyl alcohol

Active ingredient

Isopropyl alcohol 70% v/v. Purpose: Antiseptic

Purpose

Antiseptic

When using this product keep out of eyes, ears, and mouth. In case of contact with eyes, rinse eyes thoroughly with water.

Do not use

- in children less than 2 months of age
- on open skin

Stop use and ask a doctor if irritation or rash occurs. These may be signs of a serious condition.

Keep out of reach of children. If swallowed, get medical help or contact a Poison Control Center right away.

Directions

Unfold towelette, wipe hands, discard after use.

Rub thoroughly into hands for at least 30 seconds, allow to dry.

Directions

Peel back flap on front to pull out a wipe.

Unfold and wipe hands thoroughly.

Reseal and let hands dry.

No need to rinse.

Warnings

For external use only. Flammable. Keep away from heat or flame

- Do not replace wipes used for medical procedures.
- These wipes are meant for general cleansing.

Other information

Store between 15-30℃ (59-86℉)

Inactive ingredients

Purified water USP